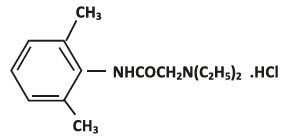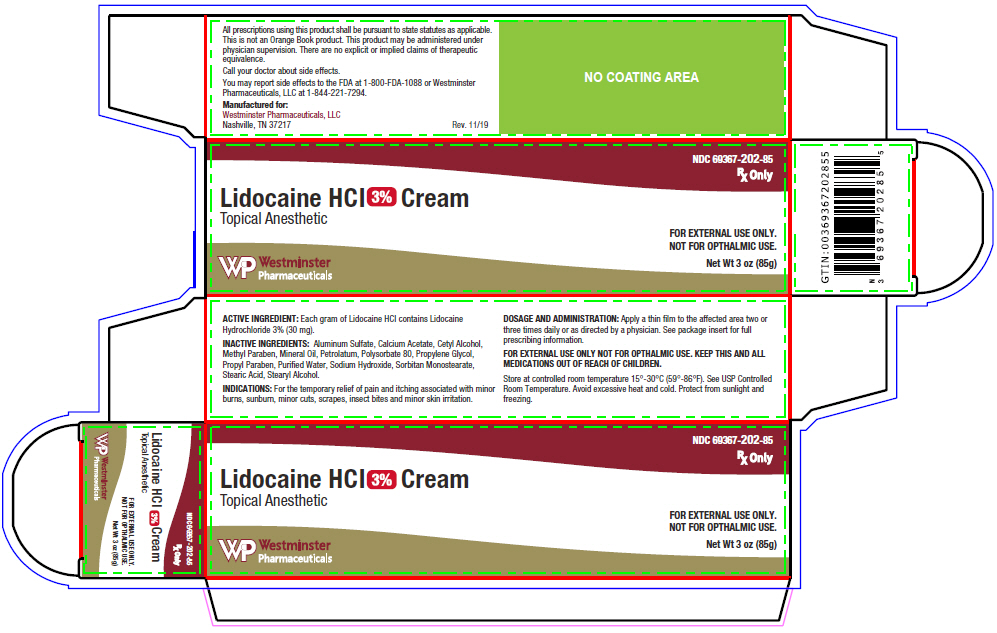 DRUG LABEL: Lidocaine hydrochloride
NDC: 69367-202 | Form: CREAM
Manufacturer: Westminster Pharmaceuticals, LLC
Category: prescription | Type: HUMAN PRESCRIPTION DRUG LABEL
Date: 20201130

ACTIVE INGREDIENTS: LIDOCAINE HYDROCHLORIDE 30 mg/1 g
INACTIVE INGREDIENTS: ALUMINUM SULFATE; CALCIUM ACETATE; CETYL ALCOHOL; METHYLPARABEN; MINERAL OIL; PETROLATUM; POLYSORBATE 80; PROPYLENE GLYCOL; PROPYLPARABEN; WATER; SODIUM HYDROXIDE; SORBITAN MONOSTEARATE; STEARIC ACID; STEARYL ALCOHOL

LIDOCAINE HCL - lidocaine hcl cream

Westminster Pharmaceuticals, LLC.

Disclaimer: This drug has not been found by FDA to be safe and effective, and this labeling has not been approved by FDA.

Prescribing Information

DESCRIPTION

Contains lidocaine HCl 3% in a mild acidic vehicle. Lidocaine is chemically designated as acetamide, 2-(diethylamino)-N-(2,6-dimethylphenyl).

C14H22N2O Mol. wt. 234.34

INGREDIENTS: Each gram of Westminster Pharmaceuticals Lidocaine HCl 3% Cream contains Lidocaine HCl USP 3% (30 mg).

Inactive ingredients include: Aluminum Sulfate, Calcium Acetate, Cetyl Alcohol, Methylparaben, Mineral Oil, Petrolatum, Polysorbate 80, Propylene Glycol, Propylparaben, Purified Water, Sodium Hydroxide, Sorbitan Monostearate, Stearic Acid, Stearyl Alcohol.

CLINICAL PHARMACOLOGY

MECHANISM OF ACTION

Westminster Pharmaceuticals Lidocaine HCl 3% Cream releases lidocaine from a mild acidic vehicle to stabilize the neuronal membrane by inhibiting the ionic fluxes required for initiation and conduction of impulses, thereby effecting local anesthetic action. A mild acidic vehicle lowers pH to increase protection against alkaline irritations and to provide a favorable environment for healing.

PHARMACOKINETICS

Lidocaine may be absorbed following topical administration to mucous membranes, its rate and extent of absorption depending upon the specific site of application, duration of exposure, concentration, and total dosage. In general, the rate of absorption of local anesthetic agents following topical application occurs most rapidly after intratracheal administration. Lidocaine is also well-absorbed from the gastrointestinal tract, but little intact drug appears in the circulation because of biotransformation of the liver.

Lidocaine is metabolized rapidly by the liver, and metabolites and unchanged drug are excreted by the kidneys. Biotransformation includes oxidative N-dealkylation, ring hydroxylation, cleavage of the amide linkage, and conjungation. N-dealkylation, a major pathway of biotransformation, yields the metabolites monoethylglycinexylidide and glycinexlidide. The pharmacological/toxicological actions of these metabolites are similar to, but less potent than, those of lidocaine. Approximately 90% of lidocaine administered is excreted in the form of various metabolites, and less than 10% is excreted unchanged.

The primary metabolite in urine is a conjugate of 4-hydroxy-2, 6-dimethylaniline. The plasma binding of lidocaine is dependent on drug concentration, and the fraction bound decreases with increasing concentration. At concentration of 1 to 4 g of free base per mL, 60 to 80 percent of lidocaine is protein bound. Binding is also dependent on the plasma concentration of the alpha-1-acid-glycoprotein.

Lidocaine crosses the blood-brain and placental barriers, presumably by passive diffusion. Studies of lidocaine metabolism following intravenous bolus injections have shown that the elimination half-life of this agent is typically 1.5 to 2 hours. Because of the rapid rate at which lidocaine is metabolized, any condition that affects liver function may alter lidocaine kinetics. The half-life may be prolonged two-fold or more in patients with liver dysfunction. Renal dysfunction does not affect lidocaine kinetics but may increase the accumulation of metabolites. Factors such as acidosis and the use of CNS stimulants and depressants affect the CNS levels of lidocaine required to produce overt systemic effects.

Objective adverse manifestations become increasingly apparent with increasing venous plasma levels above 6 g free base per mL. In the rhesus monkey arterial blood levels of 18-21 g/mL have been shown to be threshold for convulsive activity.

INDICATIONS

Indications

For the temporary relief of pain and itching associated with minor burns, sunburn, minor cuts, scrapes, insect bites, minor skin irritation, and discomfort due to pruritus ani, pruritus vulvae, hemorrhoids, anal fissures, and similar conditions of the skin and mucous membranes.

CONTRAINDICATIONS

Tuberculous or fungal lesions of skin vaccinia, varicella and acute herpes simplex and in persons who have shown hypersensitivity to any of its components. Lidocaine is contraindicated in patients with a known history of hypersensitivity to local anesthetics of the amide type.

WARNINGS

For external use only. Not for ophthalmic use. Keep out of reach of children.

PRECAUTIONS

If irritation or sensitivity occurs or infection appears, discontinue use and institute appropriate therapy. Westminster Pharmaceuticals Lidocaine HCl 3% Cream should be used with caution in ill, elderly, debilitated patients and children who may be more sensitive to the systemic effects of lidocaine.

CARCINOGENESIS, MUTAGENESIS, AND IMPAIRMENT OF FERTILITY

Studies of lidocaine in animals to evaluate the carcinogenic potential of the effect on fertility have not been conducted.

USE IN PREGNANCY

Teratogenic Effects

Teratogenic Effects; Pregnancy Category B

Reproduction studies have been performed for lidocaine in rats at doses up to 6.6 times the human dose and have revealed no evidence of harm to the fetus caused by lidocaine. There are, however, no adequate and well-controlled studies in pregnant women.

Animal reproduction studies are not always predictive of human response. General consideration should be given to this fact before administering lidocaine to women of childbearing potential, especially during early pregnancy when maximum organogenesis takes place.

NURSING MOTHERS

It is not known whether this drug is excreted in human milk. Because many drugs are excreted in human milk, caution should be exercised when this drug is administered to a nursing mother.

PEDIATRIC USE

Dosage in pediatric patients would be reduced commensurate with age, body weight and physical condition.

ADVERSE REACTIONS

During or immediately after treatment, the skin at the site of treatment may develop erythema or edema or may be the locus of abnormal sensation.

DOSAGE AND ADMINISTRATION

Apply a thin film to the affected area two or three times daily or as directed by a physician.

HOW SUPPLIED

Westminster Pharmaceuticals Lidocaine HCl 3% Cream

1 oz (28.35g) tube - NDC 69367-202-01
3 oz (85 g) tube - NDC 69367-202-85

STORAGE AND HANDLING

Store at controlled room temperature 15° - 30°C (59° - 86°F). Avoid excessive heat and cold, Protect from sunlight and freezing.

Manufactured for:
Westminster Pharmaceuticals, LLC
Nashville, TN 37217

Rev.11/19

PRINCIPAL DISPLAY PANEL - 85 g Tube Carton

NDC 69367-202-85
Rx Only

Lidocaine HCl 3% Cream
Topical Anesthetic

FOR EXTERNAL USE ONLY.
NOT FOR OPTHALMIC USE.

Westminster
Pharmaceuticals

Net Wt 3 oz (85g)